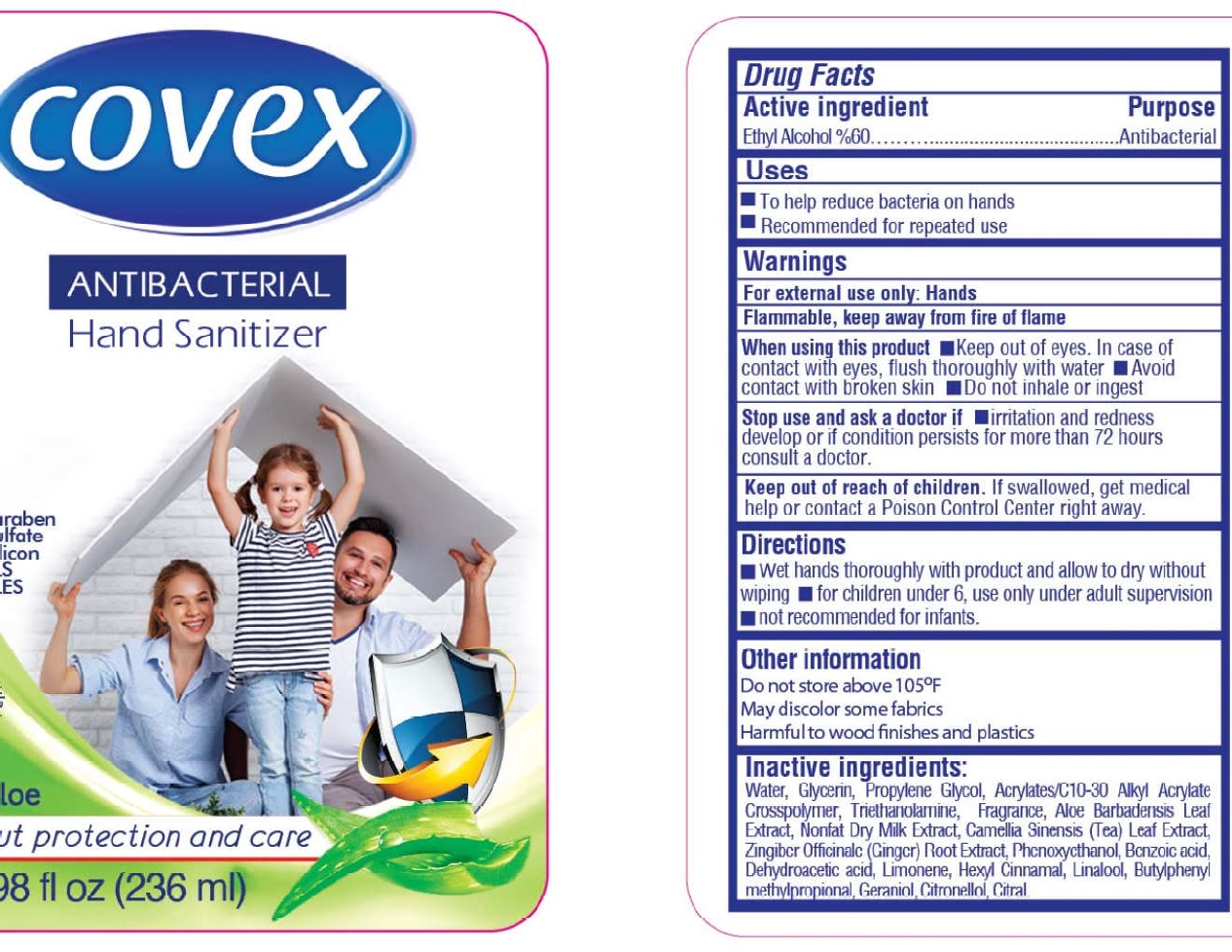 DRUG LABEL: Covex Antibacterial Hand Sanitizer, FRESH ALOE
NDC: 51209-013 | Form: GEL
Manufacturer: DALAN KIMYA ENDUSTRI ANONIM SIRKETI
Category: otc | Type: HUMAN OTC DRUG LABEL
Date: 20260122

ACTIVE INGREDIENTS: ALCOHOL 0.6 mL/1 mL
INACTIVE INGREDIENTS: WATER; GLYCERIN; PROPYLENE GLYCOL; TROLAMINE; ALOE VERA LEAF; SKIM MILK; GREEN TEA LEAF; GINGER; PHENOXYETHANOL; BENZOIC ACID; DEHYDROACETIC ACID; LIMONENE, (+)-; .ALPHA.-HEXYLCINNAMALDEHYDE; LINALOOL, (+/-)-; BUTYLPHENYL METHYLPROPIONAL; GERANIOL; .BETA.-CITRONELLOL, (R)-; CITRAL

Covex Antibacterial Hand Sanitizer, FRESH ALOE

Active ingredients

Ethyl Alcohol %60

Purpose

Antibacterial

Uses

- To help reduce bacteria on hands
- Recommended for repeated use

Warnings

For external use only: Hands

Flammable, keep away from fire of flame

When using this product.

- Keep out of eyes. In case of contact with eyes, flush thoroughly with water.
- Avoid contact with broken skin
- Do not inhale or ingest

Stop use and ask a doctor if

- irritation and redness develop or if condition persists for more than 72 hours consult a doctor.

Keep out of reach of children.

If swallowed, get medical help or contact a Poison Control Center right away.

Directions

- Wet hands thoroughly with product and allow to dry without wiping - for children under 6, use only under adult supervision - not recommended for infants.

Other information

Do not store above 105°F

May discolor some fabrics

Harmful to wood finishes and plastics

Inactive ingredients:

Water, Glycerin, Propylene Glycol, Acrylates/C10-30 Alkyl Acrylate Crosspolymer, Triethanolamine, Fragrance, Aloe Barbadensis Leaf Extract, Nonfat Dry Milk Extract, Camellia Sinensis Leaf Extract, Zingiber Officinale Root Extract, Phenoxyethanol, Benzoic acid, Dehydroacetic acid, Limonene, Hexyl Cinnamal, Linalool, Butylphenyl Methylpropional, Geraniol, Citrinellol, Citral.